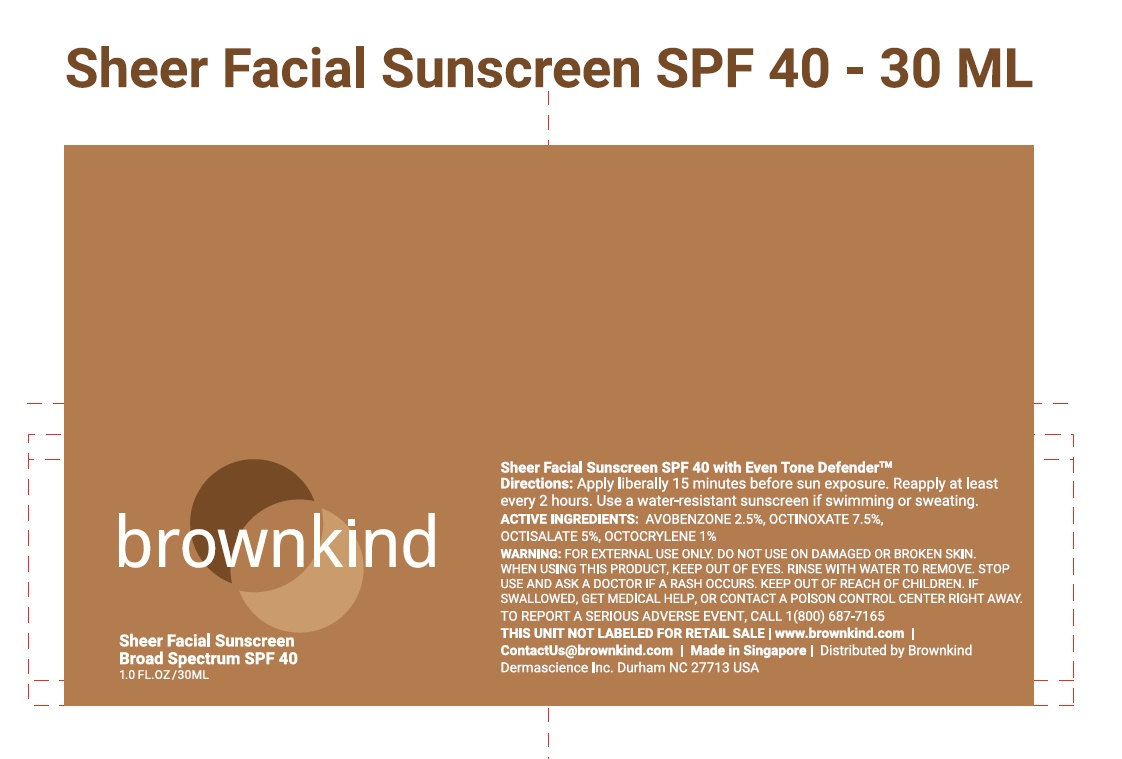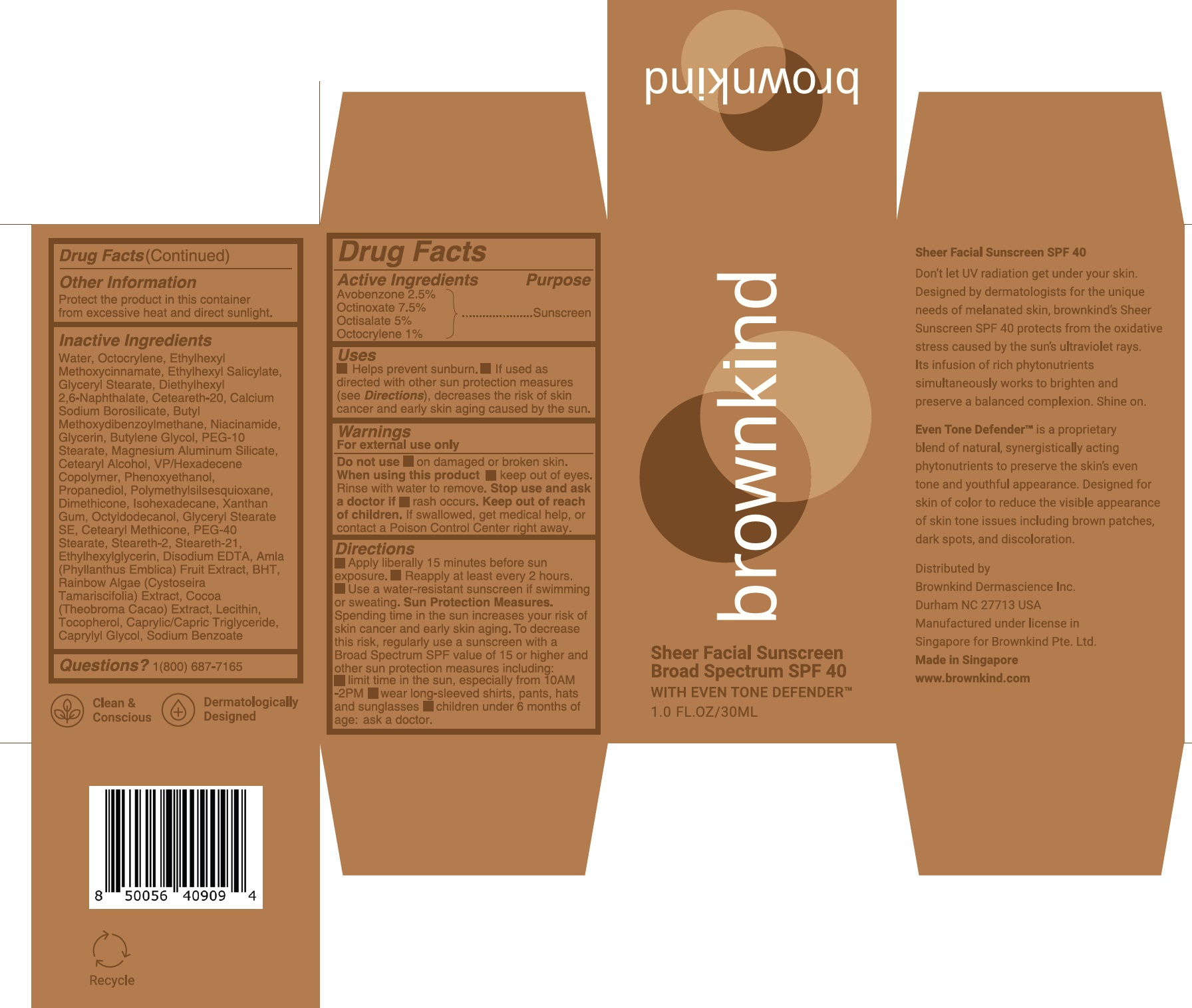 DRUG LABEL: BrushOnBlock Mineral Powder Sunscreen Broad Spectrum SPF30 Translucent
NDC: 84255-000 | Form: CREAM
Manufacturer: Brownkind Dermascience Inc.
Category: otc | Type: HUMAN OTC DRUG LABEL
Date: 20240610

ACTIVE INGREDIENTS: AVOBENZONE 25 mg/1 mL; OCTINOXATE 75 mg/1 mL; OCTISALATE 50 mg/1 mL; OCTOCRYLENE 10 mg/1 mL
INACTIVE INGREDIENTS: WATER; GLYCERYL MONOSTEARATE; DIETHYLHEXYL 2,6-NAPHTHALATE; POLYOXYL 20 CETOSTEARYL ETHER; NIACINAMIDE; GLYCERIN; BUTYLENE GLYCOL; PEG-10 STEARATE; MAGNESIUM ALUMINUM SILICATE; CETOSTEARYL ALCOHOL; VINYLPYRROLIDONE/HEXADECENE COPOLYMER; PHENOXYETHANOL; PROPANEDIOL; POLYMETHYLSILSESQUIOXANE (4.5 MICRONS); DIMETHICONE; ISOHEXADECANE; XANTHAN GUM; OCTYLDODECANOL; GLYCERYL STEARATE SE; STEARETH-2; STEARETH-21; ETHYLHEXYLGLYCERIN; EDETATE DISODIUM; PHYLLANTHUS EMBLICA FRUIT; BUTYLATED HYDROXYTOLUENE; COCOA; TOCOPHEROL; MEDIUM-CHAIN TRIGLYCERIDES; CAPRYLYL GLYCOL; SODIUM BENZOATE

Brownkind Sheer Facial Sunscreen SPF 40

Active Ingredients

Avobenzone 2.5%

Octinoxate 7.5%

Octisalate 5%

Octocrylene 1%

Purpose

Sunscreen

Uses

- Helps prevent sunburn
- if used as directed with other sun protection measures (see Directions), decreases the risk of skin cancer and early skin aging caused by the sun.

Warnings

For external use only

Do not use

- on damaged or broken skin

When using this product

- keep out of eyes. Rinse with water to remove.

Stop use and ask a doctor if

- rash occurs

Keep out of reach of children

If swallowed, get medical help or contact a Poison Control Center right away.

Directions

- Apply liberally 15 minutes before sun exposure.
- Reapply at least every 2 hours.
- Use a water-resistant sunscreen if swimming or sweating. Sun Protection Measures. Spending time in the sun increases your risk of skin cancer and early skin aging. To decrease this risk, regularly use a sunscreen with a Broad Spectrum SPF value of 15 or higher and other sun protection measures including:

- limit time in the sun, especially from 10AM-2PM
- wear long-sleeved shirts, pants, hats, and sunglasses
- children under 6 months of age: ask a doctor.

Other Information

Protect the product in this container from excessive heat and direct sunlight.

Inactive Ingredients

Water, Octocrylene, Ethylhexyl Methoxycinnamate, Ethylhexyl Salicylate, Glyceryl Stearate, Diethylhexyl 2,6-Naphthalate, Ceteareth-20, Calcium Sodium Borosilicate, Butyl Methoxydibenzoylmethane, Niacinamide, Glycerin, Butylene Glycol, PEG-10 Stearate, Magnesium Aluminum Silicate, Cetearyl Alcohol, VP/Hexadecene Copolymer, Phenoxyethanol, Propanediol, Polymethylsilsesquioxane, Dimethicone, Isohexadecane, Xanthan Gum, Octyldodecanol, Glyceryl Stearate SE, Cetearyl Methicone, PEG-40 Stearate, Steareth-2, Steareth-21,Ethylhexylglycerin, Disodium EDTA, Amla (Phyllanthus Emblica) Fruit Extract, BHT, Rainbow Algae (Cystoseira Tamariscifolia) Extract, Cocoa (Theobroma Cacao) Extract, Lecithin, Tocopherol, Caprylic/Capric Triglyceride, Caprylyl Glycol, Sodium Benzoate

Questions?

1(800) 687-7165